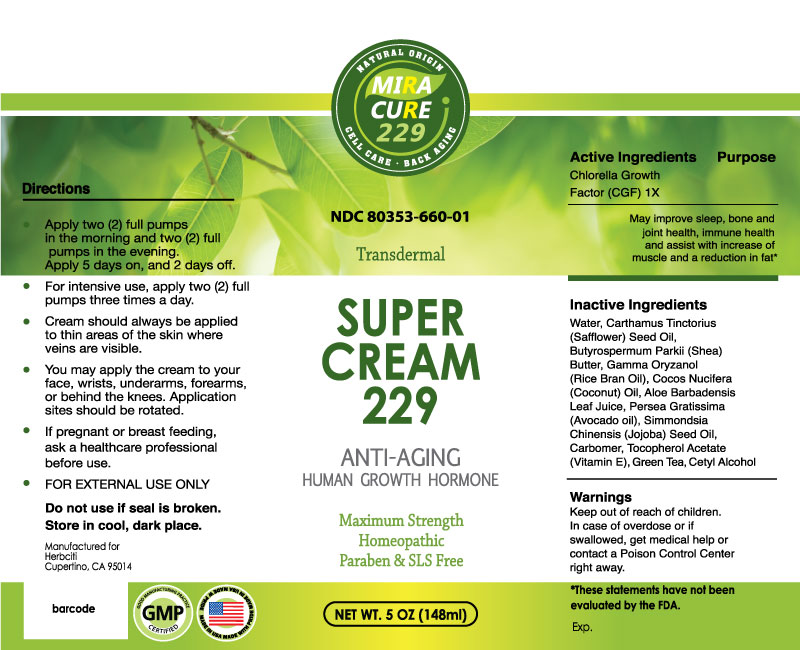 DRUG LABEL: Super Cream 229
NDC: 80353-660 | Form: CREAM
Manufacturer: HerbCiti LLC
Category: homeopathic | Type: HUMAN OTC DRUG LABEL
Date: 20210512

ACTIVE INGREDIENTS: CHLORELLA VULGARIS 1 [hp_X]/1 g
INACTIVE INGREDIENTS: GREEN TEA LEAF; GAMMA ORYZANOL; SIMMONDSIA CHINENSIS SEED; PERSEA AMERICANA LEAF; CETYL ALCOHOL; BUTYROSPERMUM PARKII (SHEA) BUTTER UNSAPONIFIABLES; CARTHAMUS TINCTORIUS (SAFFLOWER) OLEOSOMES; COCONUT OIL; CARBOMER 940; ALOE VERA LEAF; .ALPHA.-TOCOPHEROL ACETATE; WATER

Active Ingredients

Chlorella Growth Factor 1X

Purpose

May improve sleep, bone and joint health, immune health and assist with increase of muscle and a reduction in fat.

Directions

Apply 2 full pumps in the morning and 2 full pumps in the evening; 5 days on, 2 days off. For intensive use, apply 2 full pumps three times a day.

DOSAGE AND ADMINISTRATION

- Cream should always be applied to thin areas of the skin where veins are visible.
- You may apply the cream to your face, wrists, underarms, forearms or behind the knees. Application sites should be rotated.
- If pregnant or breast feeding, ask a health care professional before use.
- FOR EXTERNAL USE ONLY

Inactive Ingredients

Water, Carthamus Tinctorius (Safflower) Seed Oil, Butyrospermum Parkii (Shea) Butter, Gamma Oryzanol (Rice Bran Oil), Cocos Nucifera (Coconut) Oil, Aloe Barbadensis Leaf Juice, Persea Gratissima (Avocado oil), Simmondsia Chinensis (Jojoba) Seed Oil, Carbomer, Tocopherol Acetate (Vitamin E), Green Tea, Cetyl Alcohol

Warnings

Keep out of reach of children.

WARNINGS

In case of overdose, get medical help or contact a Poison Control Center right away.

Package Label Display

SUPER CREAM 229

Anti-Aging
Human Growth Hormone
Maximum Strength
Homeopathic
Paraben & SLS Free

Net. Wt. 5 oz. (148g)